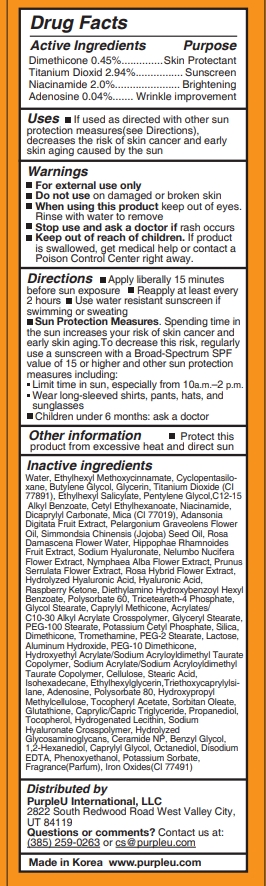 DRUG LABEL: PurpleU GLOW TONE IT LIKE SNOW
NDC: 90069-203 | Form: CREAM
Manufacturer: Purple U Co., Ltd
Category: otc | Type: HUMAN OTC DRUG LABEL
Date: 20200902

ACTIVE INGREDIENTS: ADENOSINE 0.04 g/100 mL; DIMETHICONE 0.45 g/100 mL; TITANIUM DIOXIDE 2.94 g/100 mL; NIACINAMIDE 2 g/100 mL
INACTIVE INGREDIENTS: SILICON DIOXIDE; TROMETHAMINE; PEG-2 STEARATE; LACTOSE, UNSPECIFIED FORM; ALUMINUM HYDROXIDE; SODIUM ACRYLATE/SODIUM ACRYLOYLDIMETHYLTAURATE COPOLYMER (4000000 MW); POWDERED CELLULOSE; STEARIC ACID; ISOHEXADECANE; ETHYLHEXYLGLYCERIN; OCTINOXATE; CYCLOMETHICONE 5; GLYCERIN; ALKYL (C12-15) BENZOATE; DICAPRYLYL CARBONATE; POLYSORBATE 80; HYPROMELLOSE, UNSPECIFIED; SORBITAN MONOOLEATE; MEDIUM-CHAIN TRIGLYCERIDES; TOCOPHEROL; CAPRYLYL TRISILOXANE; GLYCERYL MONOSTEARATE; HIPPOPHAE RHAMNOIDES FRUIT; NYMPHAEA ALBA FLOWER; PRUNUS SERRULATA FLOWER; 4-(P-HYDROXYPHENYL)-2-BUTANONE; POLYSORBATE 60; GLYCOL STEARATE; PEG-100 STEARATE; .ALPHA.-TOCOPHEROL ACETATE; DIETHYLAMINO HYDROXYBENZOYL HEXYL BENZOATE; TRICETEARETH-4 PHOSPHATE; JOJOBA OIL; PROPANEDIOL; ETHYLENE GLYCOL MONOBENZYL ETHER; 1,2-HEXANEDIOL; POTASSIUM CETYL PHOSPHATE; HYDROXYETHYL ACRYLATE/SODIUM ACRYLOYLDIMETHYL TAURATE COPOLYMER (100000 MPA.S AT 1.5%); TRIETHOXYCAPRYLYLSILANE; ROSA DAMASCENA FLOWER OIL; NELUMBO NUCIFERA FLOWER; GLUTATHIONE; HYDROLYZED GLYCOSAMINOGLYCANS (BOVINE; 50000 MW); CERAMIDE NP; CAPRYLYL GLYCOL; OCTANEDIOL; EDETATE DISODIUM ANHYDROUS; PHENOXYETHANOL; FERRIC OXIDE RED; WATER; BUTYLENE GLYCOL; OCTISALATE; MICA; ADANSONIA DIGITATA FRUIT; POTASSIUM SORBATE; PENTYLENE GLYCOL; PELARGONIUM GRAVEOLENS FLOWER OIL; HYDROGENATED SOYBEAN LECITHIN; CARBOMER INTERPOLYMER TYPE A (ALLYL SUCROSE CROSSLINKED); PEG-10 DIMETHICONE (600 CST); CETYL ETHYLHEXANOATE; HYALURONATE SODIUM; HYALURONIC ACID

90069-203

Active Ingredients

Dimethicone 0.45%

Titanium Dioxid 2.94%

Niacinamide 2.0%

Adenosine 0.04%

Purpose

Skin Protectant

Sunscreen

Brightening

Wrinkle improvement

Uses

If used as directed with other sun protection measures(see Directions), decreases the risk of skin cancer and early skin aging caused by the sun

Warnings

- For external use only
- Do not use on damaged or broken skin
- When using this product keep out of eyes. Rinse with water to remove

Stop use and ask a doctor if

rash occurs

Keep out of reach of children

If product is swallowed, get medical help or contact a Poison Control Center right away.

Directions

- Apply liberally 15 minutes before sun exposure
- Reapply at least every 2 hours
- Use water resistant sunscreen if swimming or sweating
- Sun Protection Measures. Spending time in the sun increases your risk of skin cancer and early skin aging.To decrease this risk, regularly use a sunscreen with a Broad-Spectrum SPF value of 15 or higher and other sun protection measures including:
- Limit time in sun, especially from 10a.m.–2 p.m.
- Wear long-sleeved shirts, pants, hats, and sunglasses
- Children under 6 months: ask a doctor

Other information

Protect this product from excessive heat and direct sun

Inactive ingredients

Water, Ethylhexyl Methoxycinnamate, Cyclopentasiloxane, Butylene Glycol, Glycerin, Titanium Dioxide (CI 77891), Ethylhexyl Salicylate, Pentylene Glycol,C12-15 Alkyl Benzoate, Cetyl Ethylhexanoate, Niacinamide, Dicaprylyl Carbonate, Mica (CI 77019), Adansonia Digitata Fruit Extract, Pelargonium Graveolens Flower Oil, Simmondsia Chinensis (Jojoba) Seed Oil, Rosa Damascena Flower Water, Hippophae Rhamnoides Fruit Extract, Sodium Hyaluronate, Nelumbo Nucifera Flower Extract, Nymphaea Alba Flower Extract, Prunus Serrulata Flower Extract, Rosa Hybrid Flower Extract, Hydrolyzed Hyaluronic Acid, Hyaluronic Acid, Raspberry Ketone, Diethylamino Hydroxybenzoyl Hexyl Benzoate, Polysorbate 60, Triceteareth-4 Phosphate, Glycol Stearate, Caprylyl Methicone, Acrylates/ C10-30 Alkyl Acrylate Crosspolymer, Glyceryl Stearate, PEG-100 Stearate, Potassium Cetyl Phosphate, Silica, Dimethicone, Tromethamine, PEG-2 Stearate, Lactose, Aluminum Hydroxide, PEG-10 Dimethicone, Hydroxyethyl Acrylate/Sodium Acryloyldimethyl Taurate Copolymer, Sodium Acrylate/Sodium Acryloyldimethyl Taurate Copolymer, Cellulose, Stearic Acid, Isohexadecane, Ethylhexylglycerin,Triethoxycaprylylsilane, Adenosine, Polysorbate 80, Hydroxypropyl Methylcellulose, Tocopheryl Acetate, Sorbitan Oleate, Glutathione, Caprylic/Capric Triglyceride, Propanediol, Tocopherol, Hydrogenated Lecithin, Sodium Hyaluronate Crosspolymer, Hydrolyzed Glycosaminoglycans, Ceramide NP, Benzyl Glycol, 1,2-Hexanediol, Caprylyl Glycol, Octanediol, Disodium EDTA, Phenoxyethanol, Potassium Sorbate, Fragrance(Parfum), Iron Oxides(CI 77491)